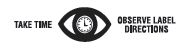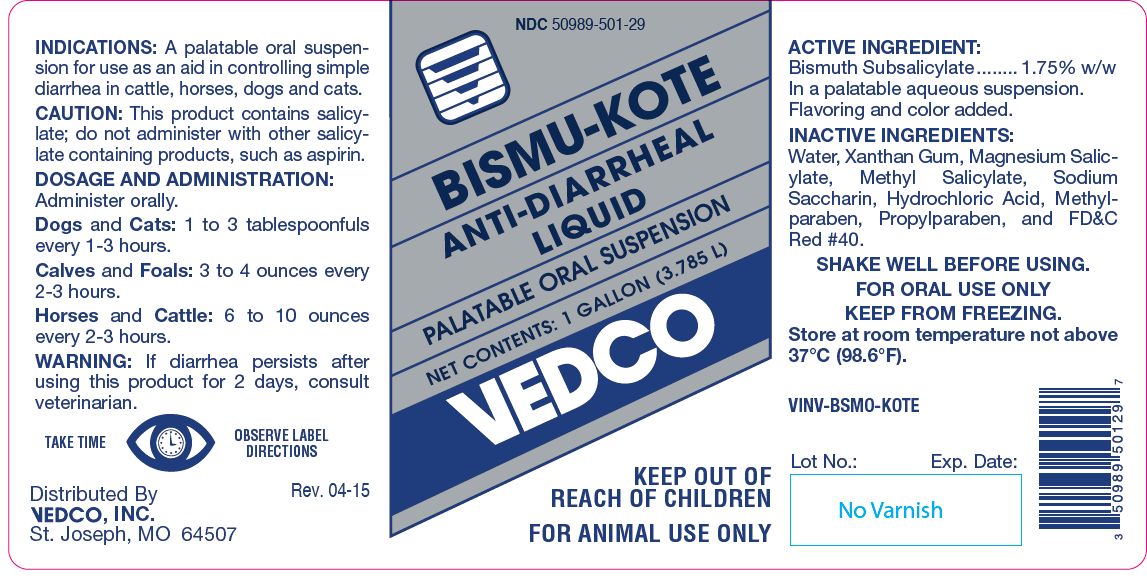 DRUG LABEL: BISMU-KOTE
NDC: 50989-501 | Form: SUSPENSION
Manufacturer: Vedco, Inc.
Category: animal | Type: OTC ANIMAL DRUG LABEL
Date: 20221114

ACTIVE INGREDIENTS: BISMUTH SUBSALICYLATE 17.4 g/1 L

BISMU-KOTE

PURPOSE

Anti-Diarrheal Liquid
Palatable Oral Suspension

KEEP OUT OF REACH OF CHILDREN
FOR ANIMAL USE ONLY

INDICATIONS:

A palatable oral suspension for use as an aid in controlling simple diarrhea in cattle, horses, dogs and cats.

CAUTION:

This product contains salicylate; do not administer with other salicylate containing products, such as aspirin.

DOSAGE AND ADMINISTRATION:

Administer orally.

Dogs and Cats: 1 to 3 tablespoonfuls every 1-3 hours.
Calves and Foals: 3 to 4 ounces every 2-3 hours.
Horses and Cattle: 6 to 10 ounces every 2-3 hours.

WARNING:

If diarrhea persists after using this product for 2 days, consult veterinarian.

ACTIVE INGREDIENT:

Bismuth Subsalicylate........ 1.75% w/w
In a palatable aqueous suspension.
Flavoring and color added.

INACTIVE INGREDIENTS:

Water, Xanthan Gum, Magnesium Salicylate, Methyl Salicylate, Sodium Saccharin, Hydrochloric Acid, Methylparaben, Propylparaben, and FD&C Red #40.

SHAKE WELL BEFORE USING.
FOR ORAL USE ONLY
KEEP FROM FREEZING.

STORAGE AND HANDLING

Store at room temperature not above 37°C (98.6°F).

NET CONTENTS:

1 GALLON (3.785 L)

INFORMATION FOR OWNERS/CAREGIVERS

Distributed By
VEDCO, INC.
St. Joseph, MO 64507

VINV-BSMO-KOTE